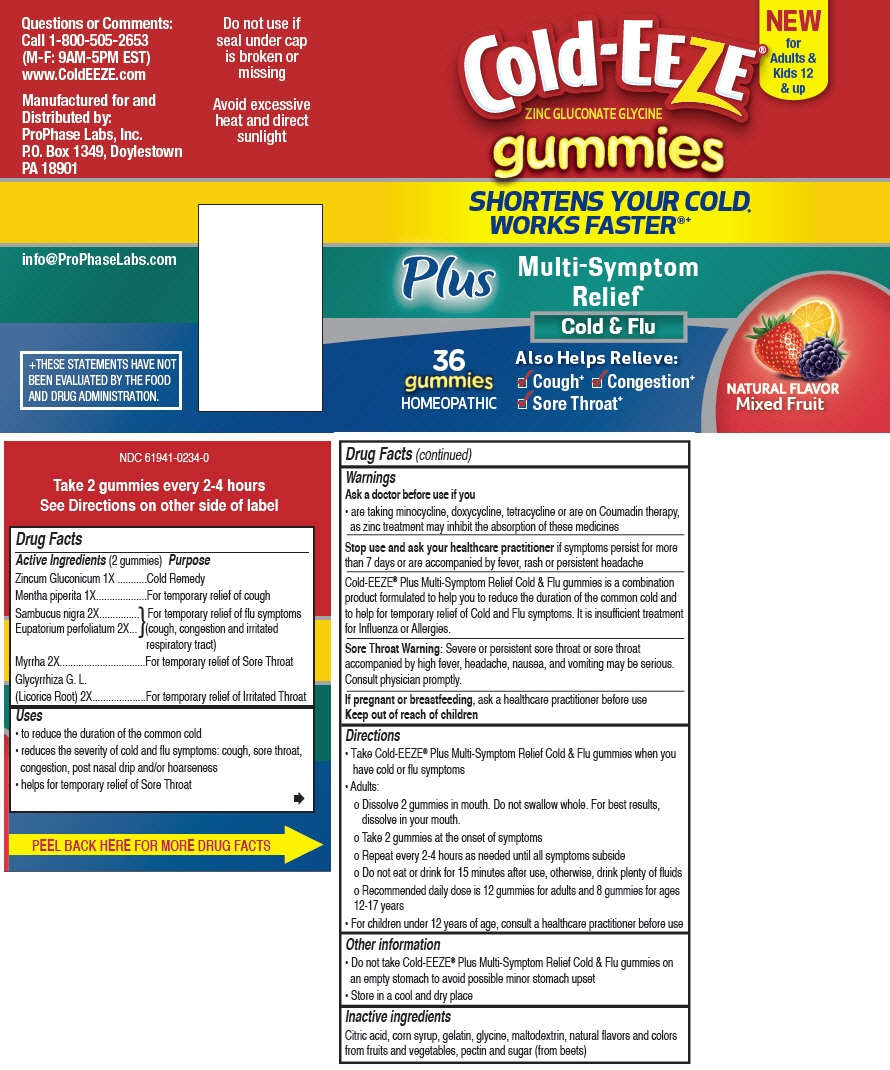 DRUG LABEL: Cold-EEZE 
NDC: 61941-0234 | Form: TABLET, ORALLY DISINTEGRATING
Manufacturer: ProPhase Labs, Inc.
Category: homeopathic | Type: HUMAN OTC DRUG LABEL
Date: 20161011

ACTIVE INGREDIENTS: Zinc Gluconate 1 [hp_X]/1 1; Mentha Piperita 1 [hp_X]/1 1; eupatorium perfoliatum flowering top 2 [hp_X]/1 1; sambucus nigra flower 2 [hp_X]/1 1; MYRRH 2 [hp_X]/1 1; GLYCYRRHIZA GLABRA LEAF 2 [hp_X]/1 1
INACTIVE INGREDIENTS: Citric Acid Monohydrate; Corn Syrup; Gelatin, Unspecified; Glycine; MALTODEXTRIN; Pectin; SUCROSE

Cold-EEZE®
Gummies Plus Multi-Symptom Relief Cold and Flu

Drug Facts

ACTIVE INGREDIENT

Active Ingredients (2 gummies) | Purpose
Zincum Gluconicum 1X | Cold Remedy
Mentha piperita 1X | For temporary relief of cough
Sambucus nigra 2X | For temporary relief of flu symptoms
Eupatorium perfoliatum 2X | (cough, congestion and irritated respiratory tract)
Myrrha 2X | For temporary relief of Sore Throat
Glycyrrhiza G. L. (Licorice Root) 2X | For temporary relief of Irritated Throat

Uses

- to reduce the duration of the common cold
- reduces the severity of cold and flu symptoms: cough, sore throat, congestion, post nasal drip and/or hoarseness
- helps for temporary relief of Sore Throat

Warnings

Ask a doctor before use if you

- are taking minocycline, doxycycline, tetracycline or are on Coumadin therapy, as zinc treatment may inhibit the absorption of these medicines

Stop use and ask your healthcare practitioner if symptoms persist for more than 7 days or are accompanied by fever, rash or persistent headache

Cold-EEZE® Plus Multi-Symptom Relief Cold & Flu gummies is a combination product formulated to help you to reduce the duration of the common cold and to help for temporary relief of Cold and Flu symptoms. It is insufficient treatment for Influenza or Allergies.

Sore Throat Warning

Severe or persistent sore throat or sore throat accompanied by high fever, headache, nausea, and vomiting may be serious. Consult physician promptly.

PREGNANCY OR BREAST FEEDING

If pregnant or breastfeeding, ask a healthcare practitioner before use

Keep out of reach of children

Directions

- Take Cold-EEZE® Plus Multi-Symptom Relief Cold & Flu gummies when you have cold or flu symptoms
- Adults:
  - Dissolve 2 gummies in mouth. Do not swallow whole. For best results, dissolve in your mouth.
  - Take 2 gummies at the onset of symptoms
  - Repeat every 2-4 hours as needed until all symptoms subside
  - Do not eat or drink for 15 minutes after use, otherwise, drink plenty of fluids
  - Recommended daily dose is 12 gummies for adults and 8 gummies for ages 12-17 years
- For children under 12 years of age, consult a healthcare practitioner before use

Other information

- Do not take Cold-EEZE® Plus Multi-Symptom Relief Cold & Flu gummies on an empty stomach to avoid possible minor stomach upset
- Store in a cool and dry place

Inactive ingredients

Citric acid, corn syrup, gelatin, glycine, maltodextrin, natural flavors and colors from fruits and vegetables, pectin and sugar (from beets)

Questions or Comments

Call 1-800-505-2653
(M-F: 9AM-5PM EST)

Distributed by:
ProPhase Labs, Inc.
P.O. Box 1349, Doylestown
PA 18901

PRINCIPAL DISPLAY PANEL - 36 gummy Bottle Label

NEW
for
Adults &
Kids 12
& up

Cold-EEZE®
ZINC GLUCONATE GLYCINE

gummies

SHORTENS YOUR COLD,
WORKS FASTER®+

Plus
Multi-Symptom
Relief
Cold & Flu

36
gummies
HOMEOPATHIC

Also Helps Relieve:

✓ Cough^+
✓ Congestion^+
✓ Sore Throat^+

NATURAL FLAVOR
Mixed Fruit